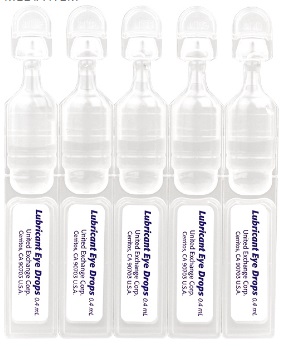 DRUG LABEL: Restore Plus Single Vial
NDC: 65923-657 | Form: SOLUTION/ DROPS
Manufacturer: United Exchange Corp.
Category: otc | Type: HUMAN OTC DRUG LABEL
Date: 20211110

ACTIVE INGREDIENTS: CARBOXYMETHYLCELLULOSE SODIUM 5 mg/1 mL
INACTIVE INGREDIENTS: SODIUM LACTATE; CALCIUM CHLORIDE; MAGNESIUM CHLORIDE; POTASSIUM CHLORIDE; WATER; SODIUM CHLORIDE; HYDROCHLORIC ACID; SODIUM HYDROXIDE

Refresh Plus Single Vial Eye Drops 0.4 ml Bulk 6577ZZ (2018)

Active ingredient Purpose

Carboxymethylcellulose sodium 0.5%.........................Eye lubricant

Uses

- For the temporary relief of burning, irritation, and discomfort due to dryness of the eye or exposure to wind or sun.
- May be used as a protectant against further irritation

Warnings

For external use only.

- to avoid contamination, do not touch tip of container to any surface. Do not reuse. Once opened, discard.
- do not touch unit-dose tip to eyes.
- if solution changes color or becomes cloudy, do not use

Stop use and ask a doctor if you experience eye pain changes in vision, continued redness or irritation of the eye, or in the condtion worsens or persists for more than 72 hours

Keep out of reach of children. If swallowed, get medical help or contact a Poison Control Center right away.

Directions

To open, twist and pull tab to remove. Instill 1 or 2 drops in the affected eye(s) as needed and discard container.

if used for post-operative (e.g. LASIK) dryness and discomfort, follow your eye doctor's instructions

Other information

- use only if single-use container is intact
- use before expiration date marked on container
- store at 59°-86°F (15°-30°C)
- retain carton for future reference

INACTIVE INGREDIENT

Inactive ingredients calcium chloride, magnesium chloride, potassium chloride, purified water, sodium chloride, and sodium lactate. May also contain hydrochloric acid and/or sodium hydroxide to adjust pH

DOSAGE AND ADMINISTRATION

Distributed by:

Wal-Mart Stores, Inc.

Bentonville, AR 72716

Made in Korea